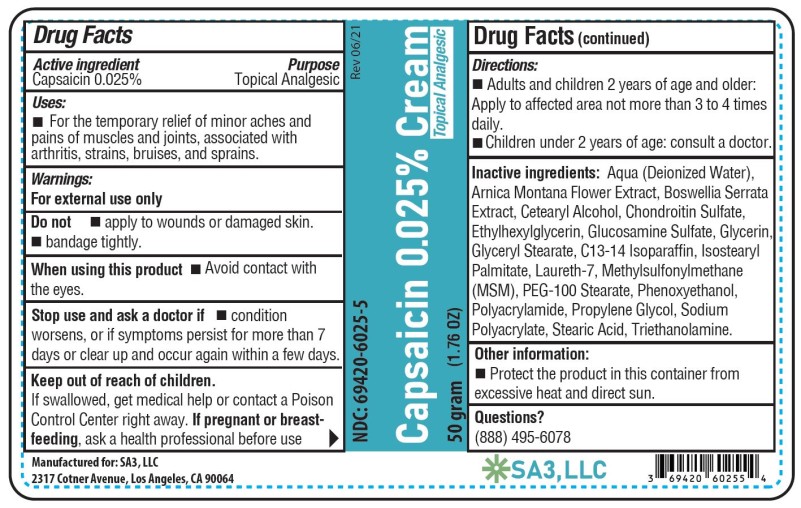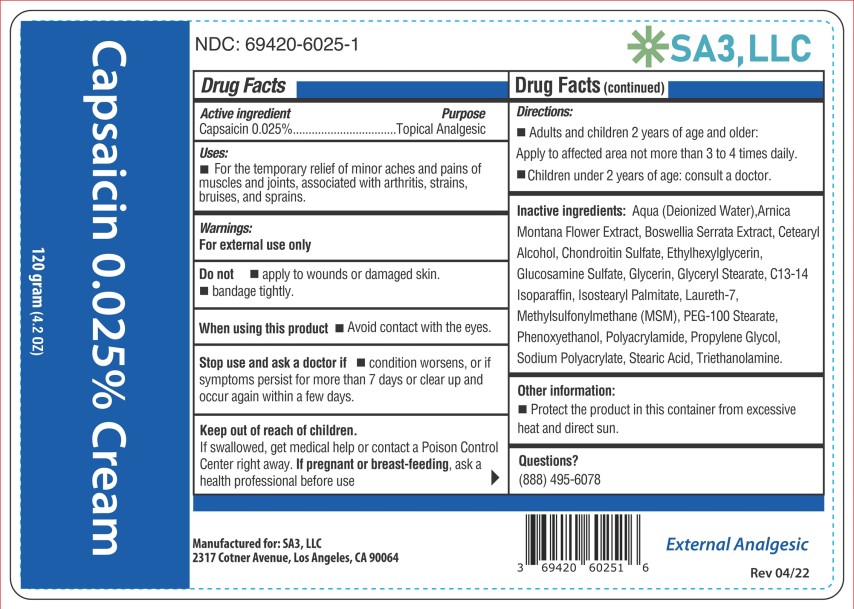 DRUG LABEL: Capsaicin
NDC: 69420-6025 | Form: CREAM
Manufacturer: SA3, LLC
Category: otc | Type: HUMAN OTC DRUG LABEL
Date: 20241209

ACTIVE INGREDIENTS: CAPSAICIN 0.025 g/100 g
INACTIVE INGREDIENTS: WATER; ARNICA MONTANA FLOWER; INDIAN FRANKINCENSE; CETOSTEARYL ALCOHOL; ETHYLHEXYLGLYCERIN; GLUCOSAMINE SULFATE; GLYCERIN; GLYCERYL MONOSTEARATE; C13-14 ISOPARAFFIN; ISOSTEARYL PALMITATE; LAURETH-7; DIMETHYL SULFONE; PEG-100 STEARATE; PHENOXYETHANOL; PROPYLENE GLYCOL; STEARIC ACID; TROLAMINE; CHONDROITIN SULFATE (BOVINE); POLYACRYLAMIDE (10000 MW); SODIUM POLYACRYLATE (2500000 MW)

Capsaicin Cream

CAPSAICIN – Capsaicin 0.025% Cream

SA3, LLC

Disclaimer: Most OTC drugs are not reviewed and approved by FDA, however they may be marketed if they comply with applicable regulations and policies. FDA has not evaluated whether this product complies.

----------

Capsaicin 0.025% Cream

Drug Facts

Active ingredient

Capsaicin 0.025%

Purpose

Topical analgesic

Uses

Temporarily relieves minor aches and pains of muscles and joints due to:

• simple backache

• arthritis

• strains

• sprains

Warnings

For external use only

Read all warnings and directions before use. Test first on small area of skin.

Do not

• Apply to wounds or damaged skin

• Bandage tightly

• If you are allergic to capsicum or chili peppers

When using this product

• You may experience a burning sensation. The intensity of this reaction varies among individuals and may be severe. With regular use, this sensation generally disappears after several days.

• Avoid contact with the eyes, lips, nose and mucous membranes

• Do not tightly wrap or bandage the treated area

• Do not apply heat to the treated area immediately before or after use

Stop use and ask a doctor if

• Condition worsens, or if symptoms persist for more than 7 days or clear up and occur again within a few days

• Severe burning persists or blistering occurs

Keep out of reach of children.

If swallowed, get medical help or contact a Poison Control Center immediately. If pregnant or breast-feeding, ask a health professional before use.

Directions

Adults and children 2 years of age and older:

Apply to affected area not more than 3 to 4 times daily. Wash hands thoroughly with soap and water immediately after application.

Children under 2 years: consult a doctor

Other information

Store at room temperature 15°-30°C (59°-86°F). Protect the product from excessive heat and direct sun.

Inactive ingredients

Aqua (Deionized Water), Arnica Montana Flower Extract, Boswellia Serrata Extract, Cetearyl Alcohol, Chondroitin Sulfate, Ethylhexylglycerin, Glucosamine Sulfate, Glycerin, Glyceryl Stearate, C13-14 Isoparaffin, Isostearyl Palmitate, Laureth-7, Methylsufonylmethane (MSM), PEG-100 Stearate, Phenoxyethanol, Polyacrylamide, Propylene Glycol, Sodium Polyacrylate, Stearic Acid, and Triethanolamine

PRINCIPAL DISPLAY PANEL

Capsaicin 0.025% cream

NDC 69420-6025-5

50 grams

SA3, LLC

PRINCIPAL DISPLAY PANEL

Capsaicin 0.025% cream

NDC 69420-6025-1

120 grams

SA3, LLC